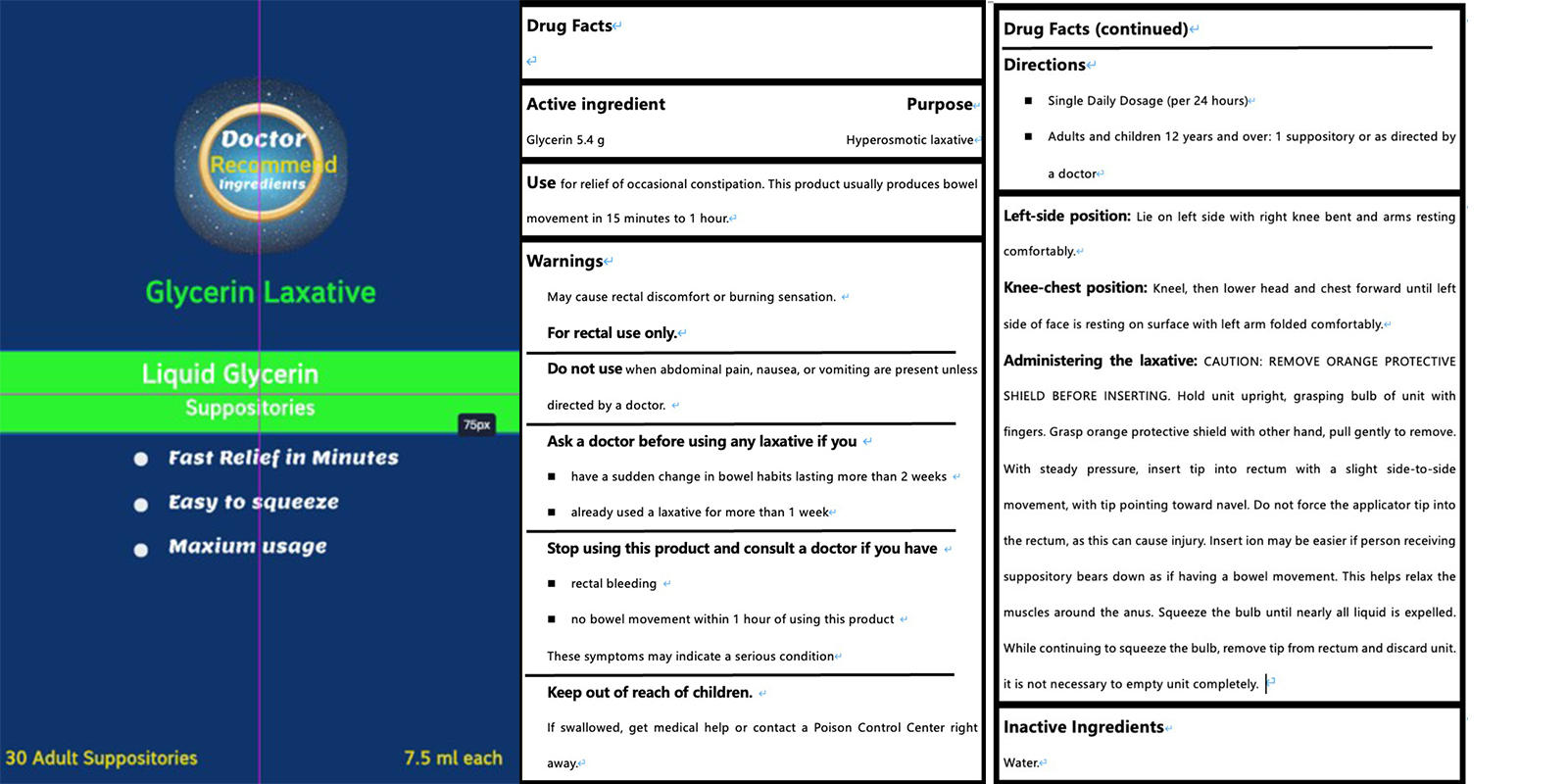 DRUG LABEL: Liquid Glycerin Laxatives
NDC: 85157-002 | Form: LIQUID
Manufacturer: Shanghai Yijing Medical Technology Co., Ltd.
Category: otc | Type: HUMAN OTC DRUG LABEL
Date: 20250219

ACTIVE INGREDIENTS: GLYCERIN 7.2 g/10 mL
INACTIVE INGREDIENTS: WATER

Liquid Glycerin Laxatives

Liquid Glycerin Laxatives

ACTIVE INGREDIENT

GLYCERIN 5.3g

PURPOSE

Hyperosmotic laxative

INDICATIONS AND USAGE

USe for relief of occasional constipation. This product usually produces bowel movement in 15 minutes to 1 hour.

WARNINGS

May cause rectal discomfort or burning sensation.
For rectal use only

Do not use when abdominal pain, nausea, or vomiting are present unless directed by a doctor.

Ask a doctor before using any laxative if you
have a sudden change in bowel habits lasting more than 2 weeks
already used a laxative for more than 1 week

STOP USE

Stop using this product and consult a doctor if you have
rectal bleeding
no bowel movement within 1 hour of using this product
These symptoms may indicate a serious condition

KEEP OUT OF REACH OF CHILDREN

If swallowed, get medical help or contact a Poison Control Center right away.

Single Daily Dosage (per 24 hours)
Adults and children 12 years and over: 1 suppository or as directed by a doctore

Left-side position: Lie on left side with right knee bent and arms resting comfortably.
Knee-chest position: Kneel, then lower head and chest forward until leftside of face is resting on surface with left arm folded comfortably. Administering the laxative: CAUTION: REMOVE ORANGE PROTECTIVESHIELD BEFORE INSERTING. Hold unit upright, grasping bulb of unit withfingers. Grasp orange protective shield with other hand, pull gently to remove.With steady pressure, insert tip into rectum with a slight side-to-sidemovement, with tip pointing toward navel. Do not force the applicator tip intothe rectum, as this can cause injury. Insert ion may be easier if person receivingsuppository bears down as if having a bowel movement. This helps relax themuscles around the anus. Squeeze the bulb until nearly all liquid is expelled.While continuing to squeeze the bulb, remove tip from rectum and discard unit.
it is not necessary to empty unit completely.

INACTIVE INGREDIENT

WATER